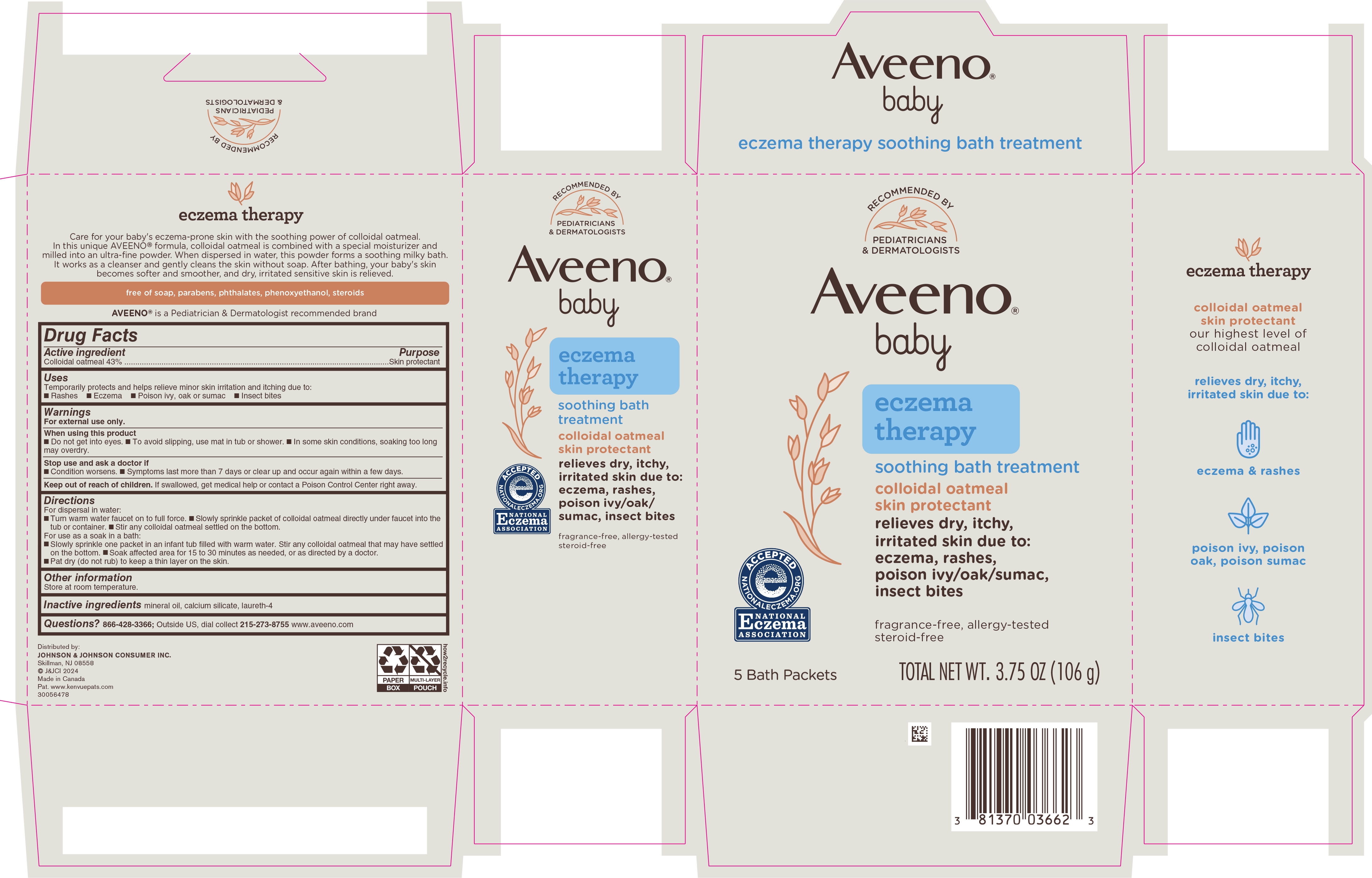 DRUG LABEL: Aveeno Baby Eczema Therapy Soothing Bath Treatment
NDC: 69968-0541 | Form: POWDER
Manufacturer: Kenvue Brands LLC
Category: otc | Type: HUMAN OTC DRUG LABEL
Date: 20250725

ACTIVE INGREDIENTS: OATMEAL 430 mg/1 g
INACTIVE INGREDIENTS: MINERAL OIL; CALCIUM SILICATE; LAURETH-4

Aveeno Baby ® Eczema Therapy SOOTHING BATH TREATMENT

Drug Facts

Active ingredient

Colloidal oatmeal 43%

Purpose

Skin protectant

Uses

Temporarily protects and helps relieve minor skin irritation and itching due to:

- Rashes
- Eczema
- Poison ivy, oak or sumac
- Insect bites

Warnings

For external use only.

When using this product

- Do not get into eyes.
- To avoid slipping, use mat in tub or shower.
- In some skin conditions, soaking too long may overdry.

Stop use and ask a doctor if

- Condition worsens.
- Symptoms last more than 7 days or clear up and occur again within a few days.

Keep out of reach of children. If swallowed, get medical help or contact a Poison Control Center right away.

Directions

For dispersal in water:

- Turn warm water faucet on to full force.
- Slowly sprinkle packet of colloidal oatmeal directly under the faucet into the tub or container.
- Stir any colloidal oatmeal settled on the bottom.

For use as a soak in a bath:

- Slowly sprinkle one packet in an infant tub filled with warm water. Stir any colloidal oatmeal that may have settled on the bottom.
- Soak affected area for 15 to 30 minutes as needed, or as directed by a doctor.
- Pat dry (do not rub) to keep a thin layer on the skin.

Other information

Store at room temperature.

Inactive ingredients

mineral oil, calcium silicate, laureth-4

Questions?

866-428-3366; Outside US, dial collect 215-273-8755 www.aveeno.com

Distributed by:
JOHNSON & JOHNSON CONSUMER INC.
Skillman, NJ 08558

PRINCIPAL DISPLAY PANEL - 106 g Packet Carton

RECOMMENDED BY

PEDIATRICIANS

& DERMATOLOGISTS

Aveeno®

baby

eczema

therapy

soothing bath treatment

colloidal oatmeal

skin protectant

relieves dry, itchy,

irritated skin due to:

eczema, rashes,

poison ivy/oak/sumac,

insect bites

fragrance-free, allergy-tested

steroid-free

ACCEPTED

e

NATIONALECZEMA.ORG

NATIONAL

ECZEMA

ASSOCIATION

5 Bath Packets

TOTAL NET WT. 3.75 OZ (106 g)